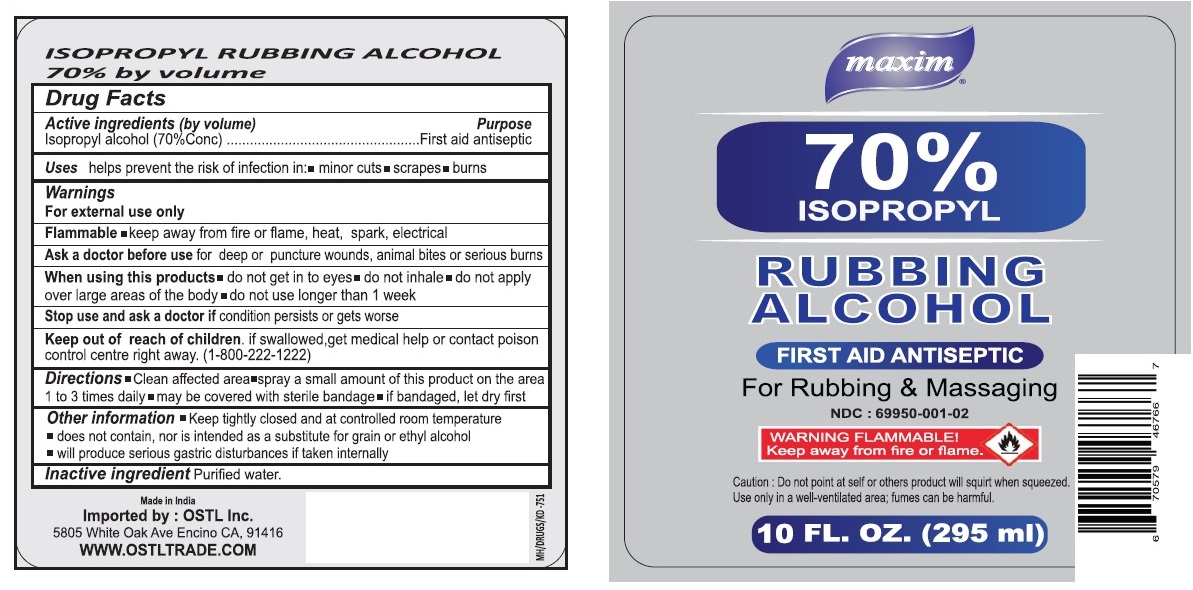 DRUG LABEL: maxim 70% ISOPROPYL RUBBING ALCOHOL
NDC: 69950-001 | Form: LIQUID
Manufacturer: OSTL, INC.
Category: otc | Type: HUMAN OTC DRUG LABEL
Date: 20191220

ACTIVE INGREDIENTS: ISOPROPYL ALCOHOL 70 mL/100 mL
INACTIVE INGREDIENTS: WATER

maxim 70% ISOPROPYL RUBBING ALCOHOL

Active ingredients (by volume)

Isopropyl alcohol (70% Conc)

Purpose

First aid antiseptic

Keep out of reach of children. If swallowed, get medical help or contact poison control centre right away. (1-800-222-1222)

INDICATIONS AND USAGE

Uses helps prevent the risk of infection in: • minor cuts • scrapes • burns

Warnings

For external use only

Flammable • keep away from fire or flame, heat, spark, electrical

Ask a doctor before use for deep or puncture wounds, animals bites or serious burns

When using this products • do not get into eyes • do not inhale • do not apply over large areas of the body • do not use longer than 1 week

Stop use and ask a doctor if condition persists or gets worse

Directions

•Clean affected area •spray a small amount of this product on the area 1 to 3 times daily •may be covered with sterile bandage
•if bandaged, let dry first

Inactive ingredient Purified water

Other information •Keep tightly closed and at controlled room temperature

• does not contain, nor is intended as a substitute for grain or ethyl alcohol

• will produce serious gastric disturbances if taken internally.

For Rubbing & Massaging

Made in India

Imported by: OSTL Inc.

5805 White Oak Ave Encino CA, 91416

WWW.OSTLTRADE.COM